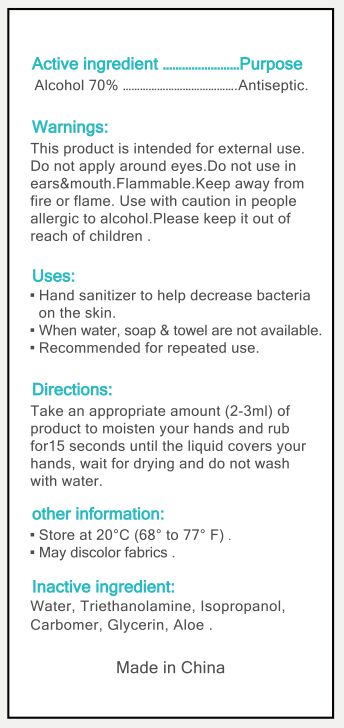 DRUG LABEL: Hand Sanitizer
NDC: 75758-001 | Form: GEL
Manufacturer: Guangzhou noval Medical Co.,Ltd.
Category: otc | Type: HUMAN OTC DRUG LABEL
Date: 20211121

ACTIVE INGREDIENTS: ALCOHOL 70 mL/100 mL
INACTIVE INGREDIENTS: WATER; CARBOMER COPOLYMER TYPE B (ALLYL PENTAERYTHRITOL CROSSLINKED); TROLAMINE; ISOPROPYL ALCOHOL

DOSAGE AND ADMINISTRATION

Take an appropriate amount (2-3ml) of product to moisten your hands and rub for 15 seconds until the liquid covers your hands, wait for drying and do not wash with water.

INACTIVE INGREDIENT

Water, trierhanolamine, glycerin, propylene gloycol, tocopheryl acetate, aloe barbadensis gel, carbomer, aloe vera.

INDICATIONS AND USAGE

Hand sanitizer to help decrease bacteria on the skin.

When water, soap & towel are not available.

Recommended for repeated use.

ACTIVE INGREDIENT

Alcohol 70%....................Antiseptic

PURPOSE

Hand sanitizer to help decrease bacteria on the skin.

When water, soap & towel are not available.

Recommended for repeated use.

WARNINGS

This product is intended for external use.

Do not take it internally,.

Use with caution in people allergic to alcohol.

Please keep it out of reach of children.